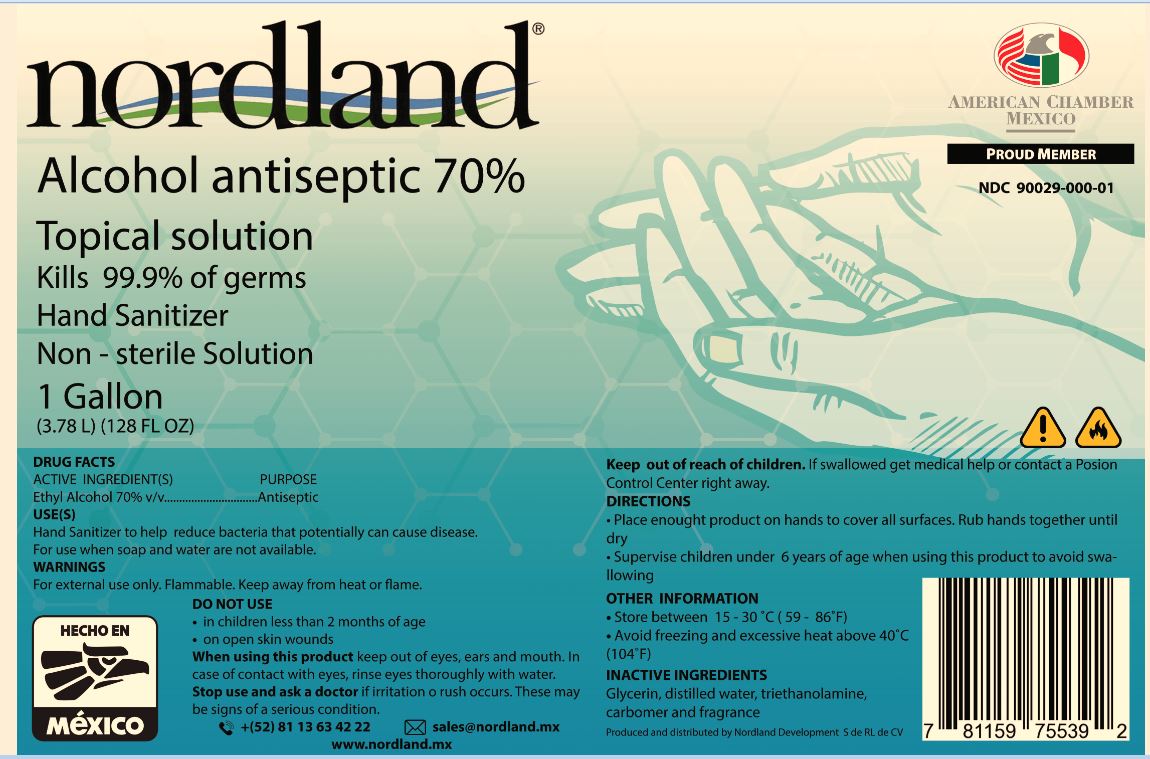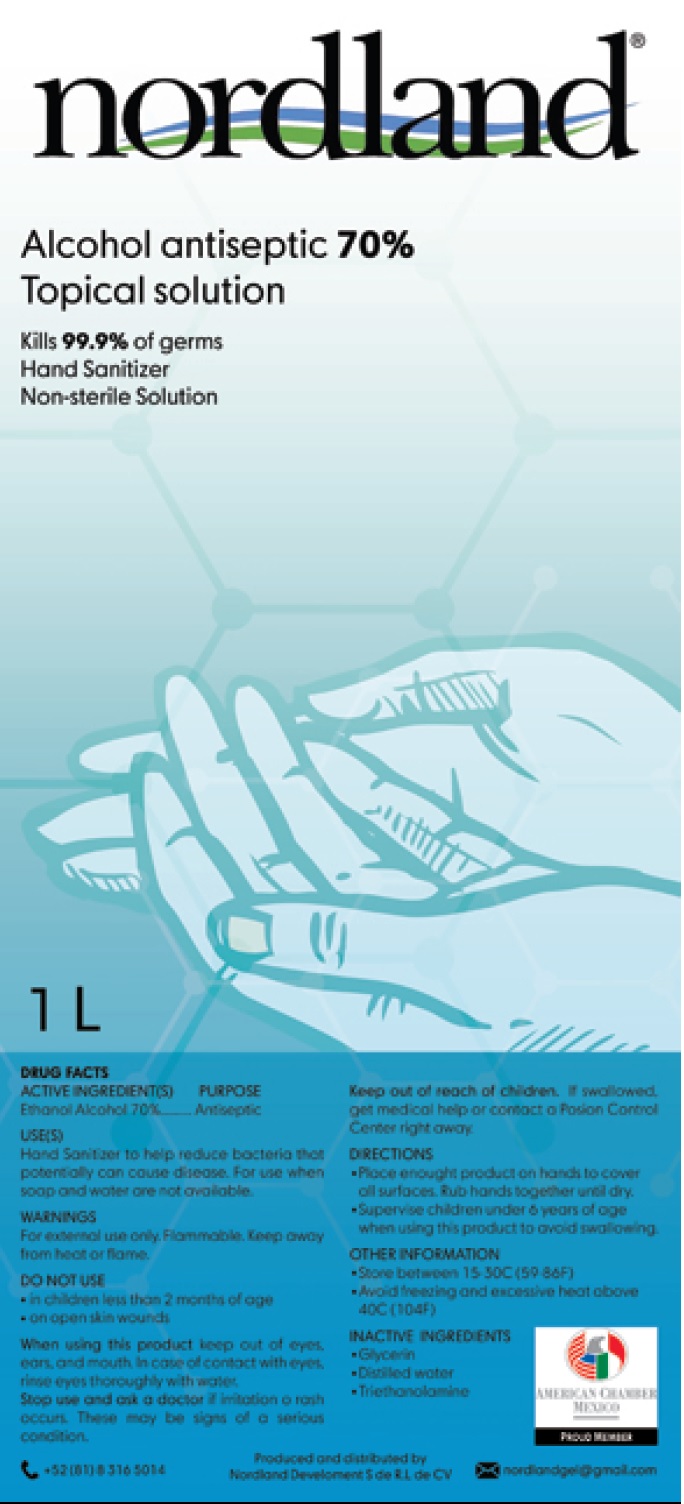 DRUG LABEL: Nordland Hand Sanitizer
NDC: 90029-000 | Form: GEL
Manufacturer: Nordland Development, S. de R.L. de C.V.
Category: otc | Type: HUMAN OTC DRUG LABEL
Date: 20200914

ACTIVE INGREDIENTS: ALCOHOL 0.7 mL/1 mL
INACTIVE INGREDIENTS: GLYCERIN; WATER; TROLAMINE; CARBOMER HOMOPOLYMER, UNSPECIFIED TYPE

Nordland Hand Sanitizer

ACTIVE INGREDIENT(S)

Ethyl Alcohol 70% v/v

PURPOSE

Antiseptic

USE(S)

Hand sanitizer to help reduce bacteria that potentially can cause disease. For use when soap and water are not available.

WARNINGS

For external use only. Flammable. Keep away from heat or flame.

DO NOT USE

in children less than 2 months of age

- on open skin wounds

When using this product

keep out of eyes, ears and mouth. In case of contact with eyes, rinse eye thoroughly with water.

Stop use and ask a doctor

if irritation or rash occurs. These may be signs of a serious condition.

Keep out of reach of children.

If swallowed, get medical help or contact a Poison Control Center right away.

DIRECTIONS

Place enough product on hands to cover

- all surfaces. Rub hand together until dry. Supervise children under 6 years of age
- when using this product to avoid swallowing.

INACTIVE INGREDIENTS

Glycerin, distilled water, triethanolamine, carbomer and fragrance